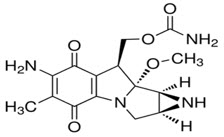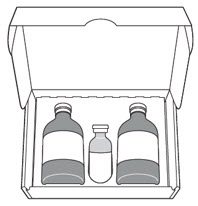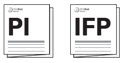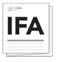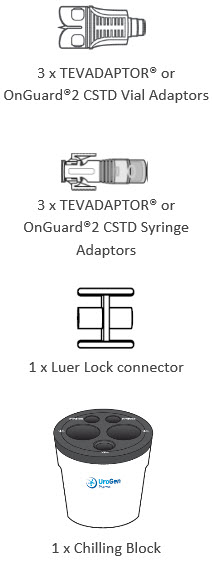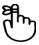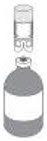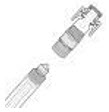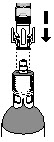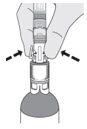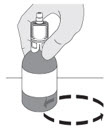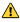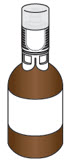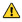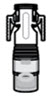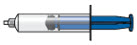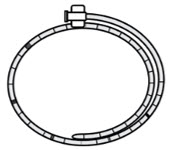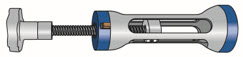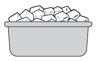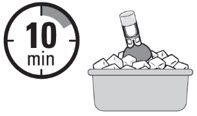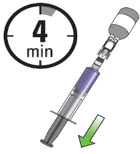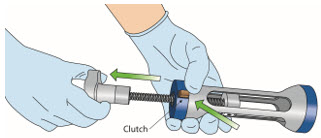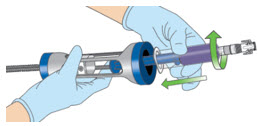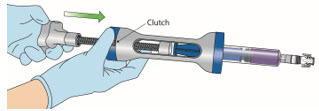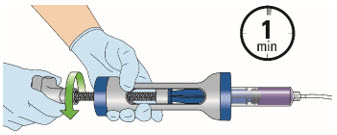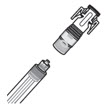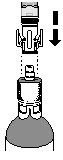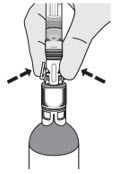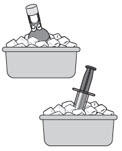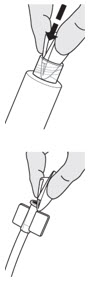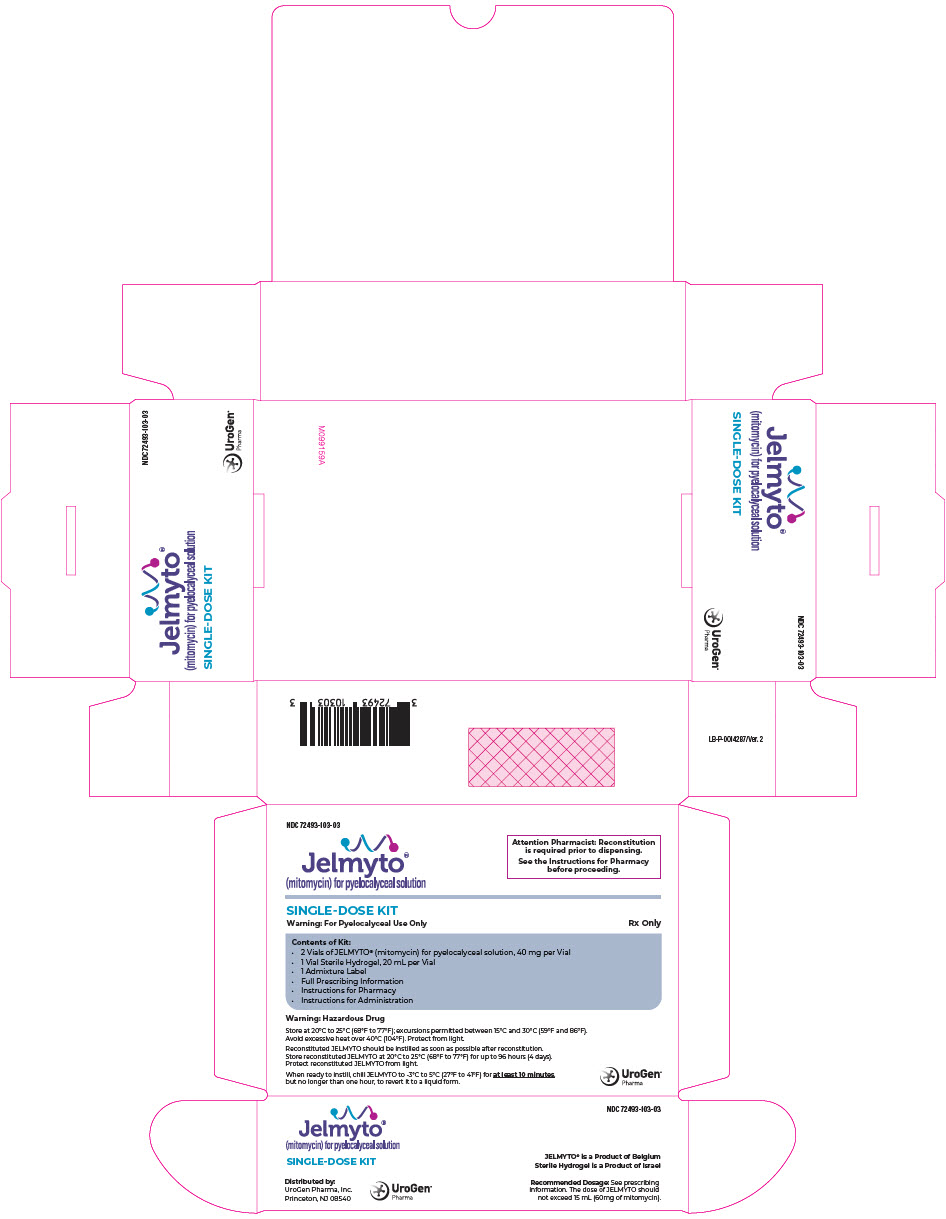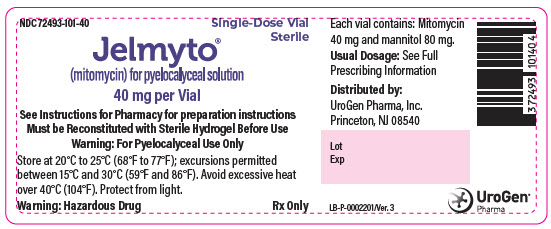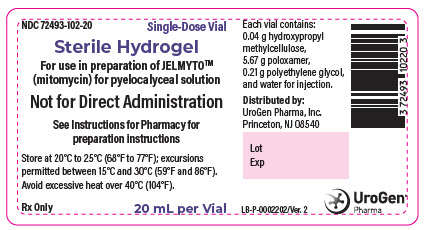 DRUG LABEL: JELMYTO
NDC: 72493-103 | Form: KIT | Route: URETERAL
Manufacturer: UroGen Pharma, Inc.
Category: prescription | Type: HUMAN PRESCRIPTION DRUG LABEL
Date: 20250709

ACTIVE INGREDIENTS: Mitomycin 40 mg/1 1
INACTIVE INGREDIENTS: Mannitol; POLOXAMER 407; POLYETHYLENE GLYCOL, UNSPECIFIED; HYPROMELLOSE, UNSPECIFIED; WATER

HIGHLIGHTS OF PRESCRIBING INFORMATION

These highlights do not include all the information needed to use JELMYTO safely and effectively. See full prescribing information for JELMYTO.
JELMYTO® (mitomycin) for pyelocalyceal solution
Initial U.S. Approval: 1974

1 INDICATIONS AND USAGE

JELMYTO is an alkylating drug indicated for the treatment of adult patients with low-grade Upper Tract Urothelial Cancer (LG-UTUC). (1)

2 DOSAGE AND ADMINISTRATION

- JELMYTO is for pyelocalyceal use only and not for intravenous use, topical use, or oral administration. (2.1)
- Administer 1.3 g of sodium bicarbonate orally the evening prior to, the morning of, and 30 minutes prior to instillation procedure (total of 3.9 g). (2.1)
- The dose of JELMYTO to be instilled is 4 mg per mL via ureteral catheter or nephrostomy tube, with total instillation volume based on volumetric measurements using pyelography, not to exceed 15 mL (60 mg of mitomycin). (2.2)
- Instill JELMYTO once weekly for six weeks. For patients with a complete response 3 months after JELMYTO initiation, JELMYTO instillations may be administered once a month for a maximum of 11 additional instillations. (2.2)

3 DOSAGE FORMS AND STRENGTHS

For pyelocalyceal solution: A kit containing the following:

- Two 40 mg (each) single-dose vials of mitomycin for pyelocalyceal solution (3)
- One vial of 20 mL sterile hydrogel for reconstitution (3)

4 CONTRAINDICATIONS

- Perforation of the bladder or upper urinary tract. (4)

5 WARNINGS AND PRECAUTIONS

- Ureteric Obstruction: Ureteric obstruction may occur. Monitor patients for signs and symptoms of ureteric obstruction. Transient or long-term ureteral stents or alternative procedures may be required. Withhold or permanently discontinue JELMYTO based on the severity of the ureteric obstruction. (5.1)
- Bone Marrow Suppression: Thrombocytopenia and neutropenia may occur. Monitor blood counts. Withhold or permanently discontinue JELMYTO based on the severity. (5.2)
- Embryo-Fetal Toxicity: Can cause fetal harm. Advise of potential risk to a fetus and to use effective contraception. (5.3, 8.1, 8.3)

6 ADVERSE REACTIONS

The most common adverse reactions (≥ 20%) are ureteric obstruction, flank pain, urinary tract infection, hematuria, renal dysfunction, nausea, abdominal pain, fatigue, dysuria, and vomiting. (6.1)

To report SUSPECTED ADVERSE REACTIONS, contact UroGen Pharma at 1-855-987-6436 or FDA at 1-800-FDA-1088 or www.fda.gov/medwatch.

8 USE IN SPECIFIC POPULATIONS

Lactation: Advise not to breastfeed. (8.2)

FULL PRESCRIBING INFORMATION

1 INDICATIONS AND USAGE

JELMYTO® is indicated for the treatment of adult patients with low-grade Upper Tract Urothelial Cancer (LG-UTUC).

2 DOSAGE AND ADMINISTRATION

2.1 Important Administration Instructions

See the Instructions for Administration provided separately.

JELMYTO is for pyelocalyceal use only. JELMYTO is not for intravenous use, topical use, or oral administration. Prior to every instillation, instruct the patient to take 1.3 g of sodium bicarbonate orally the evening prior to, the morning of, and 30 minutes prior to the instillation procedure (total of 3.9 g).

General anesthesia, local anesthesia, sedation, prophylactic antibiotics and/or antihistamines may be used at the discretion of the treating urologist. If the patient is to be anesthetized, advise the patient not to take sodium bicarbonate within 30 minutes prior to the treatment.

Consider withholding diuretics one day prior to instillation until 4 hours post-instillation.

When instilling JELMYTO, the entire syringe must be emptied within one minute.

Advise patients that JELMYTO may discolor urine to a violet to blue color following the instillation procedure. Advise patients to avoid contact with urine for at least six hours post-instillation, to void urine sitting on a toilet, and to flush the toilet several times after use.

2.2 Recommended Dosage

The dose of JELMYTO to be instilled is 4 mg per mL via ureteral catheter or a nephrostomy tube, with total instillation volume based on volumetric measurements using pyelography, not to exceed 15 mL (60 mg of mitomycin).

Instill JELMYTO once weekly for six weeks. For patients with a complete response 3 months after JELMYTO initiation, JELMYTO instillations may be administered once a month for a maximum of 11 additional instillations.

2.3 Preparation and Handling

See the Instructions for Pharmacy for preparation provided separately.

JELMYTO is a hazardous drug. Follow applicable special handling and disposal procedures.^1

JELMYTO must be prepared under chilled conditions. Once reconstituted, the admixture will have a concentration of 4 mg of mitomycin per mL and will appear as a viscous liquid for instillation. Reconstituted JELMYTO has reverse thermal properties with a gelation point of approximately 19°C (66°F). Reconstituted JELMYTO should be instilled as soon as possible after reconstitution. Store reconstituted JELMYTO at 20°C to 25°C (68°F to 77°F) for up to 96 hours (4 days). JELMYTO will appear as a semisolid gel when stored under these conditions. Protect reconstituted JELMYTO from light.

JELMYTO must be instilled as a chilled solution using a Uroject12 Lever, a Luer Lock syringe, and a ureteral catheter with molded Luer Lock connector. Once chilled at -3°C to 5°C (27°F to 41°F), JELMYTO will convert to a viscous liquid for instillation and is stable for up to 1 additional hour. Reconstituted JELMYTO must be instilled within 1 hour after it is converted to a viscous liquid.

3 DOSAGE FORMS AND STRENGTHS

For pyelocalyceal solution: A kit containing the following:

- Two 40 mg (each) single-dose vials of sterile, lyophilized, grey to greyish-purple, cake or powder of mitomycin for pyelocalyceal solution
- One single-dose vial of 20 mL of sterile, clear, colorless gel with or without bubbles at room temperature or clear, colorless liquid at 2°C to 8°C (36°F to 46°F), to be used as a vehicle for reconstitution

4 CONTRAINDICATIONS

JELMYTO is contraindicated in patients with perforation of the bladder or upper urinary tract.

5 WARNINGS AND PRECAUTIONS

5.1 Ureteric Obstruction

Ureteric obstruction, including ureteral stenosis and hydronephrosis, occurred in patients receiving JELMYTO.

In the Olympus study, ureteric obstruction was reported in 58% (n=41) of patients receiving JELMYTO, including 17% (n=12) of patients who experienced Grade 3 obstruction. The median time to first onset was 72 days (range: 15-462). Interventions in the 41 patients experiencing ureteric obstruction included ureteral stent placement (88%), balloon dilatation (29%), and nephroureterectomy (4.9%). In the 36 patients who required ureteral stent placement, the median duration of indwelling stents was 52 days (range: 1-292). Ureteric obstruction did not resolve or resolved with sequelae in 44% (n=18) of these patients. Of the 41 patients who experienced ureteric obstruction, 17% (n=7) experienced Grades 1-2 increase in serum creatinine.

In the 42 patients who only received JELMYTO during the treatment phase (no maintenance therapy), ureteric obstruction was reported in 40% (n=17).

Monitor patients for signs and symptoms of ureteric obstruction, including flank pain, and fever, and for changes in renal function. Patients who experience obstruction may require transient or long-term ureteral stents or alternative procedures. Withhold or permanently discontinue JELMYTO based on the severity of ureteric obstruction.

5.2 Bone Marrow Suppression

The use of JELMYTO can result in bone marrow suppression, particularly thrombocytopenia and neutropenia. In the Olympus study, Grade 3 thrombocytopenia occurred in three patients, Grade 3 anemia in one patient, and Grade 3 neutropenia in one patient. Gross extravasation of JELMYTO via urinary tract perforation or impaired mucosa was not observed in these patients. The following tests should be obtained prior to each treatment: Platelet count, white blood cell count differential and hemoglobin. Withhold JELMYTO for Grade 2 thrombocytopenia or neutropenia. Permanently discontinue for Grade 3 or greater thrombocytopenia or neutropenia.

5.3 Embryo-Fetal Toxicity

Based on findings in animals and mechanism of action, JELMYTO can cause fetal harm when administered to a pregnant woman. In animal reproduction studies, administration of mitomycin resulted in teratogenicity. Advise females of reproductive potential to use effective contraception during treatment with JELMYTO and for 6 months following the last dose. Advise male patients with female partners of reproductive potential to use effective contraception during treatment with JELMYTO and for 3 months following the last dose [see Use in Specific Populations (8.1, 8.3) and Clinical Pharmacology (12.1)].

6 ADVERSE REACTIONS

The following clinically significant adverse reactions are discussed in greater detail in other sections of the labeling:

- Ureteric Obstruction [see Warnings and Precautions (5.1)]
- Bone Marrow Suppression [see Warnings and Precautions (5.2)]

6.1 Clinical Trials Experience

Because clinical trials are conducted under widely varying conditions, adverse reaction rates observed in clinical trials of a drug cannot be directly compared to rates in the clinical trials of another drug and may not reflect rates observed in practice.

The safety of JELMYTO was evaluated in Olympus, an open-label, single-arm study in 71 patients with LG-UTUC [see Clinical Studies (14)]. For the 71 patients treated with JELMYTO during the treatment period, the median number of instillations was 6 (range: 3-6). Following initial treatment, 29 patients were treated with up to 11 doses of maintenance instillations, with a median of 6 instillations (range: 1-11).

Serious adverse reactions occurred in 39% of patients who received JELMYTO. Serious adverse reactions in > 3% of patients included ureteric obstruction (including ureteric stenosis and hydronephrosis), flank pain, and urosepsis. Two deaths occurred due to cerebrovascular accident and failure to thrive.

JELMYTO was permanently discontinued due to an adverse reaction in 17 (24%) patients, including 11 patients who discontinued during the treatment phase and 6 who discontinued during the maintenance phase. Adverse reactions resulting in study drug discontinuation of JELMYTO in > 3% of patients who received JELMYTO included ureteric obstruction.

Dosage interruptions due to an adverse reaction occurred in 37% of patients who received JELMYTO. Adverse reactions requiring dosage interruption in > 3% of patients who received JELMYTO included renal dysfunction, ureteric obstruction, urinary tract infection, and flank pain.

The most common adverse reactions (≥ 20%) reported were ureteric obstruction, flank pain, urinary tract infection, hematuria, renal dysfunction, nausea, abdominal pain, fatigue, dysuria, and vomiting.

Table 1 summarizes the adverse reactions in Olympus.

Table 1: Adverse Reactions (≥ 10% All Grades) in Patients Who Received JELMYTO in Olympus
 | JELMYTO [Graded per National Cancer Institute Common Terminology Criteria for Adverse Events. Version 5.0 (NCI CTCAE v5)] (n=71)
Adverse Reaction | All Grades (%) | Grade 3-4 (%)
Renal and urinary disorders
Ureteric Obstruction [Includes hydronephrosis, obstructive uropathy, pelvi-ureteric obstruction, ureteric obstruction, ureteric stenosis, and urinary tract obstruction.] | 58 | 17
Ureteric stenosis | 44 | 9
Hydronephrosis | 18 | 6
Urinary tract obstruction | 7 | 1.4
Pelvi-ureteric obstruction | 6 | 1.4
Ureteric obstruction | 2.8 | 1.4
Obstructive uropathy | 1.4 | 0
Flank pain [Includes flank pain and back pain.] | 41 | 2.8
Hematuria [Includes hematuria and hemorrhage urinary tract.] | 34 | 2.8
Urinary tract infection [Includes urinary tract infection, pyelonephritis, and urinary tract infection fungal.] | 34 | 4.2
Renal dysfunction [Includes renal impairment, acute kidney injury, and renal failure.] | 25 | 2.8
Dysuria | 23 | 0
Pollakiuria | 14 | 0
Gastrointestinal disorders
Nausea | 25 | 1.4
Abdominal pain [Includes abdominal pain and abdominal pain lower.] | 24 | 1.4
Vomiting | 20 | 4.2
General disorders and administration site conditions
Fatigue [Includes asthenia, fatigue, and malaise.] | 24 | 1.4
Pyrexia | 13 | 1.4
Chills | 11 | 0
Blood and lymphatic system disorders
Anemia | 14 | 1.4
Skin and subcutaneous tissue disorders
Rash [Includes rash, dermatitis allergic, rash generalized, genital rash, eczema, rash maculo-papular, and skin exfoliation.] | 14 | 0
Pruritus | 13 | 0
Metabolism and nutrition disorders
Decreased appetite | 10 | 0
Vascular disorders
Hypertension | 10 | 4.2

Selected clinically relevant adverse reactions in < 10% and ≥ 2% of patients who received JELMYTO in Olympus include urinary tract inflammation, bladder spasm, urosepsis, hypersensitivity, and instillation site pain.

Table 2 summarizes the laboratory abnormalities in Olympus.

Table 2: Select Laboratory Abnormalities (≥ 10%) Worsening from Baseline in Patients Who Received JELMYTO in Olympus
Laboratory Abnormality [Graded per National Cancer Institute Common Terminology Criteria for Adverse Events. Version 5.0 (NCI CTCAE v5). Each test incidence is based on the number of patients who had both baseline and at least one on-study laboratory measurement available.] | JELMYTO
Laboratory Abnormality [Graded per National Cancer Institute Common Terminology Criteria for Adverse Events. Version 5.0 (NCI CTCAE v5). Each test incidence is based on the number of patients who had both baseline and at least one on-study laboratory measurement available.] | All Grades (%) | Grade ≥ 3 (%)
Hematology
Anemia | 38 | 0
Lymphopenia | 21 | 2.9
Thrombocytopenia | 21 | 2.8
Chemistry
Estimated Glomerular Filtration Rate (eGFR) [eGFR calculated per MDRD (Modification of Diet in Renal Disease) equation] | 38 | 11
Creatinine increased | 34 | 0
Hypoalbuminemia | 28 | 2.8
Hypocalcemia | 16 | 0
Hyperuricemia | 16 | 16
Hyperkalemia | 13 | 1.4
Hypernatremia | 11 | 0

8 USE IN SPECIFIC POPULATIONS

8.1 Pregnancy

Risk Summary

Based on findings in animals and mechanism of action, JELMYTO can cause fetal harm when administered to a pregnant woman [see Clinical Pharmacology (12.1)]. There are no available data on JELMYTO use in pregnant women to inform the drug-associated risk. In animal reproduction studies, administration of mitomycin resulted in teratogenicity (see Data). Advise pregnant women of the potential risk to a fetus.

The estimated background risk of major birth defects and miscarriage for the indicated population is unknown. In the U.S. general population, the estimated background risk of major birth defects and miscarriage in clinically recognized pregnancies is 2% - 4% and 15% - 20%, respectively.

Data

Animal Data

Teratological changes have been noted with mitomycin in animal studies.

8.2 Lactation

Risk Summary

There are no data on the presence of mitomycin in human milk, the effects on the breastfed child, or the effects on milk production. Because of the potential for serious adverse reactions in a breastfed child, advise women not to breastfeed during treatment with JELMYTO and for 1 week following the last dose.

8.3 Females and Males of Reproductive Potential

JELMYTO can cause fetal harm when administered to pregnant women [see Use in Specific Populations (8.1)].

Pregnancy Testing

Verify pregnancy status in females of reproductive potential prior to initiating JELMYTO.

Contraception

Females

Advise females of reproductive potential to use effective contraception during treatment with JELMYTO and for 6 months following the last dose.

Males

Advise male patients with female partners of reproductive potential to use effective contraception during treatment with JELMYTO and for 3 months following the last dose.

8.4 Pediatric Use

Safety and efficacy in pediatric patients have not been established.

8.5 Geriatric Use

Of the total number of patients in the Olympus trial, 75% (53 patients) were 65 years of age and over and 37% (26 patients) were 75 years of age and over. Clinical studies of JELMYTO did not include sufficient numbers of younger patients less than 65 years old to determine whether they respond differently from older patients.

8.6 Renal Impairment

No data are available in patients with severe renal impairment. Avoid use of JELMYTO in patients with a Glomerular Filtration Rate of < 30 mL/min.

11 DESCRIPTION

Mitomycin (also known as mitomycin-C) is an alkylating drug isolated from the broth of Streptomyces. Mitomycin is a blue-violet crystalline powder with a molecular formula of C15H18N4O5, and a molecular weight of 334.33. Its chemical name is 7-amino-9α-methoxymitosane, and it has the following structural formula:

Mitomycin is heat stable, has a high melting point, and is freely soluble in organic solvents.

JELMYTO is supplied in a kit containing two vials of sterile lyophilized mitomycin for pyelocalyceal solution, 40 mg each, and one vial of 20 mL of sterile hydrogel, to be used as a vehicle for reconstitution.

Mitomycin for pyelocalyceal solution is a sterile, lyophilized, grey to greyish-purple, cake or powder that contains mitomycin 40 mg and mannitol 80 mg in each vial.

Sterile hydrogel is a sterile, clear, colorless gel with or without bubbles at room temperature or clear, colorless liquid at 2°C to 8°C (36°F to 46°F), which contains 0.04 g hydroxypropyl methylcellulose, 5.67 g poloxamer, 0.21 g polyethylene glycol, and water for injection in each vial.

Once reconstituted, JELMYTO is a clear, purple, viscous liquid at 2°C to 8°C (36°F to 46°F) or semisolid gel at room temperature with a concentration of 4 mg per mL of mitomycin, which may contain a few visible particles and have a pH between 6.0 and 8.0.

12 CLINICAL PHARMACOLOGY

12.1 Mechanism of Action

Mitomycin inhibits the synthesis of deoxyribonucleic acid (DNA). The guanine and cytosine content correlates with the degree of mitomycin-induced cross-linking. At high concentrations of the drug, cellular RNA and protein synthesis are also suppressed.

12.2 Pharmacodynamics

There is insufficient data to characterize an exposure-response relationship or time course of pharmacodynamic response for mitomycin.

12.3 Pharmacokinetics

Absorption

The systemic exposure of mitomycin following instillation of up to 60 mg of mitomycin as JELMYTO into the pyelocalyceal system was evaluated pre-instillation and hourly for up to six hours post-instillation in six patients. The concentrations of mitomycin in plasma were variable and ranged from 2.43 to 12.80 ng/mL over the course of treatment; the mean Cmax was 6.24 ng/mL, which is estimated to be less than 1% of the expected Cmax after intravenous administration.

Elimination

Following instillation into the pyelocalyceal system, JELMYTO forms a semisolid gel which dissolves from normal kidney urine flow releasing mitomycin for up to 4 to 6 hours. Mitomycin is eliminated unchanged in the urine. Systemically absorbed mitomycin is rapidly cleared from the serum and approximately 10% is excreted unchanged in the urine.

Metabolism

Mitomycin is metabolized primarily in the liver, but metabolism occurs in other tissues as well. It is believed that the rate of clearance is inversely proportional to the maximal serum concentration because of saturation of the degradative pathways.

13 NONCLINICAL TOXICOLOGY

13.1 Carcinogenesis, Mutagenesis, Impairment of Fertility

Adequate long-term studies in animals to evaluate carcinogenic potential from instillation of mitomycin into the pyelocalyceal system have not been conducted. Mitomycin has been found to be carcinogenic in rats and mice. At doses approximating the recommended intravenous clinical dose in humans, mitomycin produced a greater than 100% increase in tumor incidence in male Sprague-Dawley rats, and a greater than 50% increase in tumor incidence in female Swiss mice.

The effect of JELMYTO on fertility is unknown.

14 CLINICAL STUDIES

The efficacy of JELMYTO is based on the results of the Olympus study (NCT02793128), an open-label, single-arm, multicenter trial that enrolled 71 patients with treatment-naïve or recurrent non-invasive low-grade upper tract urothelial cancer (LG-UTUC) with at least one measurable papillary tumor 5 to ≤ 15 mm located above the ureteropelvic junction; patients who had larger tumors could have had tumor debulking prior to treatment, in order to meet the criteria. Patients were excluded from the trial for a history of carcinoma in situ (CIS) in the urinary tract, invasive urothelial carcinoma within 5 years, high grade papillary urothelial carcinoma within 2 years; or for BCG treatment within 6 months of JELMYTO treatment. Following biopsy and prior to treatment, patients were required to have at least one remaining visible tumor with a diameter of at least 5 mm.

Patients received JELMYTO 4 mg per mL via ureteral catheter or nephrostomy tube with total instillation volume based on individualized volumetric measurements using pyelography with the intent to fill the renal pelvis. Patients were treated with 6 instillations once a week. Patients who maintained a complete response (CR) after the initial treatment period were allowed to proceed to the follow-up period. During the initial treatment period, 71 patients were treated with JELMYTO, of whom 41 were subsequently continued in the follow-up period. During the follow-up period, 29 patients received at least one dose of maintenance therapy.

The baseline demographic and disease characteristics for the trial population were: median age 71 years (range: 42-87 years); 68% male; 87% White; 90% Eastern Cooperative Oncology Group Performance Status (ECOG PS) 0 or 1 and 10% ECOG PS 2. The median number of papillary lesions subsequent to debulking and/or biopsy and prior to treatment was 1 lesion (range: 1, 5), the median diameter of the largest lesion was 8.0 mm (range: 5.0, 15.0), and the median total visible tumor burden was 10.0 mm (range: 5.0, 25.0). Twenty-six (37%) patients underwent tumor debulking during the six weeks preceding enrollment. Of 71 enrolled patients, 48% had tumors located in regions not amenable to endoscopic resection. General anesthesia was used in 37% of patients for at least one instillation during the treatment period and for 83% of patients for at least one instillation during the follow-up period.

The major efficacy outcome measures were CR and durability of CR at 12 months after determination of CR based on ureteroscopic and local pathology assessment. CR was defined as complete absence of tumor lesions in the ipsilateral pyelocalyceal system at 3 months after initiation of JELMYTO by urine cytology and ureteroscopy. Biopsy was performed if warranted. Durability of response in patients with a CR was evaluated at 3, 6, 9 and 12 months following the initial assessment. Assessment of durability of CR subsequent to these evaluations was performed per local standards of care.

Forty-one patients (58%) achieved CR in the study (95% CI: 45%, 69%). Of the 41 patients who achieved CR, 23 (56%) of the patients remained at CR at the 12-month time point for assessment of durability, 8 (20%) experienced recurrence of disease, and 10 (24%) were unable to be evaluated (died, discontinued from the study, or were indeterminate for ongoing response). The median duration of response was not reached (range: 0, 18.8 months and ongoing). One patient, who achieved 6 months of durable CR, was diagnosed with metastatic urothelial carcinoma approximately 4.5 months after the last dose of study medication and died from the disease.

15 REFERENCES

1. "OSHA Hazardous Drugs." OSHA. http://www.osha.gov/SLTC/hazardousdrugs/index.html

16 HOW SUPPLIED/STORAGE AND HANDLING

16.1 How Supplied

JELMYTO kit – NDC 72493-103-03

JELMYTO is available in a kit containing the following:

- Two 40 mg (each) single-dose vials of mitomycin for pyelocalyceal solution supplied as a sterile, lyophilized, grey to greyish-purple, cake or powder. (NDC 72493-101-40)
- One 20 mL single-dose vial of sterile hydrogel supplied as a sterile, clear, colorless gel with or without bubbles at room temperature or clear, colorless liquid at 2°C to 8°C (36°F to 46°F), to be used as a vehicle for reconstitution. (NDC 72493-102-20)

16.2 Storage and Handling

Store the JELMYTO kit at 20°C to 25°C (68°F to 77°F); excursions permitted between 15°C and 30°C (59°F and 86°F) [see USP Controlled Room Temperature]. Avoid excessive heat over 40°C (104°F). Protect from light.

JELMYTO is a hazardous drug. Follow applicable special handling and disposal procedures.^1

17 PATIENT COUNSELING INFORMATION

Advise the patient to read the FDA-approved patient labeling (Patient Information).

Ureteric Obstruction

Inform patients that ureteric obstruction may occur, and ureteral stents or alternative procedures may be required during treatment with JELMYTO. Advise patients to contact their healthcare provider immediately if signs and symptoms of ureteric obstruction, including flank pain and/or fever, occur [see Warnings and Precautions (5.1)].

Bone Marrow Suppression

Inform patients that JELMYTO may decrease blood counts such as white blood cells and platelets. Thus, it is important that periodic assessment of their blood counts be performed to detect the development of neutropenia and thrombocytopenia [see Warnings and Precautions (5.2)].

Embryo-Fetal Toxicity

Advise pregnant women and females of reproductive potential of the potential risk to a fetus. Advise females to inform their healthcare providers of a known or suspected pregnancy [see Warnings and Precautions (5.3) and Use in Specific Populations (8.1)].

Advise females of reproductive potential to use effective contraception during treatment with JELMYTO and for 6 months following the last dose [see Use in Specific Populations (8.3)].

Advise male patients with female partners of reproductive potential to use effective contraception during treatment with JELMYTO and for 3 months following the last dose [see Use in Specific Populations (8.3)].

Lactation

Advise women not to breastfeed during treatment with JELMYTO and for 1 week following the last dose [see Use in Specific Populations (8.2)].

Important Post-Treatment Instructions [see Dosage and Administration (2.1)]

Advise patients that JELMYTO contains mitomycin which is a violet to blue color and may discolor urine following the instillation procedure.

Advise patients to avoid contact with urine for at least six hours post-instillation.

Advise patients to void sitting on a toilet, flush the toilet several times after use, and to wash hands, perineum or glans with soap and water after each instillation procedure.

Advise patients to wash clothing soiled with urine promptly and separately from other clothing.

Distributed by:
UroGen Pharma, Inc.
Princeton, NJ 08540

JELMYTO® and UroGen® are registered trademarks of UroGen Pharma, Ltd.
U.S. Patent Nos. 9,040,074 and 9,950,069
Copyright© 2025 UroGen Pharma, Inc.
All rights reserved.

JEL-PI-005

Patient Information
JELMYTO® (jel-MYE-toe)
(mitomycin)
for pyelocalyceal solution

What is JELMYTO?
JELMYTO is a prescription medicine used to treat adults with a type of cancer of the lining of the upper urinary tract including the kidney called low-grade Upper Tract Urothelial Cancer (LG-UTUC).
It is not known if JELMYTO is safe and effective for use in children.

Who should not receive JELMYTO?
Do not receive JELMYTO if you have a hole or tear (perforation) of your bladder or upper urinary tract.

Before receiving JELMYTO, tell your healthcare provider about all your medical conditions, including if you:

- are pregnant or plan to become pregnant. JELMYTO can harm your unborn baby. You should not become pregnant during treatment with JELMYTO. Tell your healthcare provider right away if you become pregnant or think you may be pregnant during treatment with JELMYTO.
  Females who are able to become pregnant:
  - Your healthcare provider will check to see if you are pregnant before starting treatment with JELMYTO.
  - You should use effective birth control (contraception) during treatment with JELMYTO and for 6 months after the last dose.
  - Talk to your healthcare provider if you have questions about birth control options that are right for you.
  Males being treated with JELMYTO:
  - If you have a female partner who is able to become pregnant, you should use effective birth control (contraception) during treatment with JELMYTO and for 3 months after the last dose.
- are breastfeeding or plan to breastfeed. It is not known if JELMYTO passes into your breast milk. Do not breastfeed during treatment with JELMYTO and for 1 week after the last dose.

Tell your healthcare provider about all the medicines you take, including prescription and over-the-counter medicines, vitamins, and herbal supplements. Know the medicines you take. Keep a list of them to show to your healthcare provider and pharmacist when you get a new medicine.
Especially tell your healthcare provider if you take water pills (diuretic).

How will I receive JELMYTO?

- Your healthcare provider will tell you to take a medicine called sodium bicarbonate before each JELMYTO treatment. Your healthcare provider will provide instructions about how and when to take sodium bicarbonate.
- JELMYTO will be given to you by your healthcare provider.
- You will receive JELMYTO 1 time a week for 6 weeks. It is important that you receive all 6 doses of JELMYTO according to your healthcare provider's instructions. Your healthcare provider may recommend up to an additional 11 monthly doses.
- If you miss any appointments, call your healthcare provider as soon as possible to reschedule your appointment.
- JELMYTO is given to your kidney through a tube called a catheter.
- During treatment with JELMYTO, your healthcare provider may tell you to take additional medicines or change how you take your current medicines. Ask your healthcare provider if you have any questions.

After receiving JELMYTO:

- JELMYTO may cause your urine color to change to a violet to blue color.
- Avoid contact between your skin and urine for at least 6 hours.
- To urinate, males and females should sit on a toilet and flush the toilet several times after you use it.
- After going to the bathroom, wash your hands, your inner thighs, and genital area well with soap and water.
- Clothing that comes in contact with urine should be washed right away and washed separately from other clothing.

What are the possible side effects of JELMYTO?
JELMYTO may cause serious side effects, including:

- Swelling and narrowing of the tube that carries urine from the kidney to the bladder (ureteric obstruction). If you develop swelling and narrowing, and to protect your kidney from damage, your healthcare provider may recommend the placement of a small plastic tube (stent) in the ureter to help the kidney drain. Tell your healthcare provider right away if you develop side pain or fever during treatment with JELMYTO.
- Bone marrow problems. JELMYTO can affect your bone marrow and can cause a decrease in your white blood cell, red blood cell, and platelet counts. Your healthcare provider will do blood tests prior to each treatment to check your blood cell counts during treatment with JELMYTO. Your healthcare provider may need to temporarily or permanently stop JELMYTO if you develop bone marrow problems during treatment with JELMYTO.

The most common side effects of JELMYTO include:

- urinary tract infection
- blood in your urine
- side pain
- nausea
- trouble with urination

- kidney problems
- vomiting
- tiredness
- stomach (abdomen) pain

Call your doctor for medical advice about side effects. You may report side effects to FDA at 1-800-FDA-1088.
You can also report side effects to UroGen Pharma at 1-855-987-6436.

General information about JELMYTO.
Medicines are sometimes prescribed for purposes other than those listed in this Patient Information leaflet. You can ask your pharmacist or healthcare provider for information about JELMYTO that is written for healthcare professionals.

What are the ingredients of JELMYTO?
Active ingredient: mitomycin
Inactive ingredients: hydroxypropyl methylcellulose, mannitol, poloxamer, polyethylene glycol, and water for injection

Distributed by:
UroGen Pharma, Inc.
Princeton, NJ 08540

JELMYTO® and UroGen® are registered trademarks of UroGen Pharma, Ltd.
U.S. Patent Nos. 9,040,074 and 9,950,069
Copyright© 2022 UroGen Pharma, Inc.
All rights reserved.

JEL-PPI-003
For more information go to www.JELMYTO.com or call 1-855-987-6436.

This Patient Information has been approved by the U.S. Food and Drug Administration.

Revised: 09/2022

INSTRUCTIONS FOR PHARMACY (IFP) JELMYTO® (jel-MYE-toe) (mitomycin) for pyelocalyceal solution

Purpose of this Instructions for Pharmacy

This Instructions for Pharmacy contains information on how to prepare JELMYTO using pharmacy supplies and a Chilling Block.

Intended Use of JELMYTO

JELMYTO (mitomycin) for pyelocalyceal solution is indicated for the treatment of adult patients with low-grade Upper Tract Urothelial Cancer (LG-UTUC).

Important Information You Need to Know Before Reconstituting JELMYTO

Once reconstituted with sterile hydrogel, JELMYTO will appear as a semisolid gel. Once chilled, JELMYTO will convert to a viscous liquid.

Reconstituted JELMYTO must be prepared under chilled conditions. A Chilling Block can be used for this purpose. JELMYTO cannot be prepared without the Chilling Block or other means of chilling.

Preparation of JELMYTO must be performed under aseptic conditions.

Storage Conditions and Handling

Instill the JELMYTO solution as soon as possible after reconstitution. Store reconstituted JELMYTO at 20°C to 25°C (68°F to 77°F) for up to 96 hours (4 days). Protect from light.

JELMYTO is a cytotoxic anti-cancer drug. Procedures for Proper Handling and Disposal of anti-cancer drugs should be followed.

Supplies Needed:

JELMYTO Kit containing:

- 2 Vials of Mitomycin for Pyelocalyceal Solution, 40 mg/vial
- 1 Vial Sterile Hydrogel, 20 mL/vial
- 1 JELMYTO Admixture Label
- JELMYTO Full Prescribing Information (PI)
- JELMYTO Instructions for Pharmacy (IFP)
- JELMYTO Instructions for Administration (IFA)

Pharmacy Supplies
(Provided by Your Facility)
Do not substitute any of these components.

- 3 × TEVADAPTOR® or OnGuard®2 CSTD Vial Adaptors
- 3 × TEVADAPTOR® or OnGuard®2 CSTD Syringe Adaptors
- 1 × Luer Lock connector
- 2 × 10 mL Luer Lock syringes
- 1 × 20 mL Luer Lock syringe
- 1 × 20-25G needle (for drawing up sterile water)
- 2 mL sterile water
- 70% Isopropyl alcohol or equivalent
- 1 × Light protective bag
- 1 × Chilling Block (device design may vary)

Note: The day before your preparation, put the Chilling Block in the freezer at -20°C to -12°C (-4°F to 10.4°F) overnight. Please refer to the Chilling Block Instructions for Use for more information.

Steps to Prepare JELMYTO Admixture

A. Freeze Chilling Block
  The day before preparation, put the Chilling Block in the freezer at -20°C to -12°C (-4°F to 10.4°F) overnight.
  Note: Please refer to the Chilling Block Instructions for Use for additional information.
B. Prepare Supplies
  1. Remove the Chilling Block from the freezer.
  2. Disinfect the Chilling Block with 70% Isopropyl alcohol or equivalent, as per your pharmacy's policy. Allow it to air dry, and then place it upright inside the hood or isolator.
  3. Wait 20 minutes before continuing.
  4. Connect vial adaptors to all three vials.
  5. Connect a syringe adaptor to one of the 10 mL syringes.
  6. Connect a syringe adaptor to the 20 mL syringe.
  7. Place the three vials, the 10 mL syringe, and the 20 mL syringe into the Chilling Block for at least 10 minutes.
  8. While the vials and syringes are in the Chilling Block, withdraw 2 mL of sterile water into the other 10 mL syringe and set aside for later use.
C. Create Pre-Wetting Solution (PWS)
  1. Slowly fill the chilled 20 mL syringe with 14 mL of sterile hydrogel.
  2. Recap the chilled 20 mL syringe and place it in the Chilling Block.
  3. Slowly fill the chilled 10 mL syringe with 4 mL of sterile hydrogel.
  4. Discard the unused portion of sterile hydrogel.
  5. Replace the needle on 2 mL sterile water syringe with the Luer Lock connector.
  6. Remove the syringe adaptor from the 4 mL sterile hydrogel syringe.
  7. Connect the 4 mL sterile hydrogel syringe to the other side of the Luer Lock connector on the 2 mL sterile water syringe.
  8. Gently mix the sterile water with the sterile hydrogel by pushing the plungers back and forth at least 25 times to create the "pre-wetting solution" (PWS).
  9. Transfer the 6 mL PWS into one of the syringes.
  10. Replace the Luer Lock connector on the 6 mL PWS syringe with a new syringe adaptor.
  11. Place the 6 mL PWS syringe in the Chilling Block.
D. Mix the Admixture
  1. Remove both JELMYTO vials from the Chilling Block.
  2. Gently tap the bottom of each vial on the table to ensure all the mitomycin powder is at the bottom of the vials.
  3. Remove the chilled 6 mL PWS syringe from the Chilling Block.
  4. Inject 3 mL of PWS into each JELMYTO vial.
    Note: To ensure accurate dosing, the contents of each vial must be the same.
  5. Discard the empty PWS syringe.
  6. Gently swirl each JELMYTO vial upright at least 15 times, ensuring all powder and admixture is contained at the bottom of the vial.
    Note: Do not invert or shake the vials.
  7. Immediately remove the chilled 14 mL sterile hydrogel syringe from the Chilling Block.
  8. Immediately inject 7 mL of sterile hydrogel into each JELMYTO vial.
    Note: To ensure accurate dosing, the contents of each vial must be the same.
  9. Gently swirl each JELMYTO vial upright at least 15 times, ensuring all admixture is contained at the bottom of the vial.
    Note: Do not invert or shake the vials.
  10. Recap and place the 20 mL syringe in the Chilling Block.
  11. Mix the JELMYTO admixture vials:
    - Recap and place both JELMYTO vials in the Chilling Block for five minutes.
    - Remove both vials and vigorously swirl them upright at least 15 times, ensuring all admixture is contained at the bottom of the vials.
    - Place both vials back in the Chilling Block.
    - Repeat these steps every five minutes for a total of 30 minutes.
    Note: Do not invert or shake the vials.
E. Prepare Admixture Vial
  1. Remove one JELMYTO vial from the Chilling Block.
  2. Vigorously swirl the vial upright at least 15 times.
    Note: Do not invert or shake the vial.
  3. Using the chilled 20 mL syringe, slowly withdraw 7 mL of admixture from the vial.
    Note: If you are having difficulty withdrawing the admixture, place the components back in the Chilling Block until the admixture liquifies again.
  4. Discard the empty JELMYTO vial.
  5. Remove the remaining JELMYTO vial from the Chilling Block.
  6. Inject the contents of the 20 mL syringe into that vial. Now all the admixture is contained in one vial.
  7. Recap the vial adaptor.
  8. Vigorously swirl the vial upright at least 15 times.
    Note: Do not invert or shake the vial.
  9. Your JELMYTO admixture vial is now complete, with a resultant concentration of 4 mg of mitomycin per mL following reconstitution.
F. Dispense Admixture Vial
  1. Write the "Discard after" date and time on the supplied admixture label and apply to the prepared JELMYTO admixture vial. You may also substitute your pharmacy's label for dispensing the admixture.
    Note: The "Discard after" date and time is 96 hours (4 days) from the completion of the preparation at room temperature.
  2. Place the JELMYTO admixture vial in a light-protective bag.
  3. Transport to the treatment facility along with the JELMYTO Instructions for Administration.

Important to Remember

- All components must be kept cold during the preparation process by placing them in the Chilling Block when they are not in use.
- If you have difficulty pushing the solution or withdrawing the solution at any time, put the components back in the Chilling Block until the product liquifies.

Frequently Asked Questions:

How do I connect the vial adaptor?
Place the vial adaptor over the vial and press down firmly. You will hear a snap which confirms successful attachment.

How do I connect the syringe adaptor?
Screw the Luer Lock end of the syringe adaptor onto the syringe hub until it is finger tight.

How do I connect the syringe adaptor to the vial adaptor?
Place the syringe adaptor over the vial adaptor and align the tabs, then press down firmly. You will hear a snap which confirms successful attachment.

How do I disconnect the syringe adaptor from the vial adaptor?
Pinch the tabs on the syringe adaptor to separate it from the vial adaptor.

Do I need to put the caps on the syringes and vials before placing them back into the chilling block?
YES, the chilling block inserts are not sterile. It is important to maintain aseptic technique.

Do I have to keep the vials upright when mixing? If so, why?
YES, the vials should be upright during all mixing to ensure the contents are fully mixed at the bottom of the vial.

I am having difficulty working with the drug product. It seems to be solidifying.
If you are having difficulty pushing the solution or withdrawing the solution, place the components back into the Chilling Block until the product liquifies.

This "Instructions for Pharmacy" has been approved by the U.S. Food and Drug Administration.

Distributed by:

UroGen Pharma, Inc.
Princeton, NJ 08540
www.JELMYTO.com

JELMYTO® and UroGen® are registered trademarks of UroGen Pharma, Ltd.
TEVADAPTOR® is a registered trademark of Simplivia Healthcare Ltd.
OnGuard® is a registered trademark of B. Braun Medical Inc.

Copyright© 2022 UroGen Pharma, Inc.
All rights reserved.

JEL-IFP-003

IFP-0002025/Ver. 4

INSTRUCTIONS FOR ADMINISTRATION (IFA) JELMYTO® (jel-MYE-toe) (mitomycin) for pyelocalyceal solution For Pyelocalyceal Instillation Only

Read and follow this Instructions for Administration prior to each JELMYTO instillation.

Purpose of this Instructions for Administration

This Instructions for Administration contains information on how to instill JELMYTO using the reconstituted JELMYTO vial which you received from the pharmacy and the devices listed under Supplies Needed, obtained by your facility.

Intended Use of JELMYTO

JELMYTO (mitomycin) for pyelocalyceal solution is indicated for the treatment of adult patients with low-grade Upper Tract Urothelial Cancer (LG-UTUC).

Important Information You Need to Know Before Instilling JELMYTO

JELMYTO must be reconstituted by a healthcare professional prior to instillation. Reconstituted JELMYTO will appear as a semisolid gel. Once chilled, JELMYTO will convert to a viscous liquid for instillation.

Once instilled into the patient's pyelocalyceal system, JELMYTO will fill and conform to the cavity and become a gel, thereby exposing the tissue to mitomycin over a prolonged period of time.

JELMYTO is viscous, even when it is a liquid in a chilled state. Therefore, you will need a Uroject12 Syringe Lever to instill JELMYTO into the patient. You cannot instill JELMYTO without the Uroject12 device.

Reconstituted JELMYTO should be instilled as soon as possible after reconstitution. Store reconstituted JELMYTO at 20°C to 25°C (68°F to 77°F) for up to 96 hours (4 days). Protect from light.

When ready to instill, chill JELMYTO to 27°F to 41°F (-3°C to 5°C) for at least 10 minutes, but no longer than one hour, to revert it to a liquid form. See the Steps A through E for complete administration instructions.

JELMYTO is a cytotoxic anti-cancer drug. Procedures for Proper Handling and Disposal of anti-cancer drugs should be followed.

Supplies Needed:

One vial of reconstituted JELMYTO, with a resultant concentration of 4 mg of mitomycin per mL following reconstitution.

(prepared and provided by the pharmacy)

JELMYTO vial

Ancillary Supplies:

(to be provided by your facility)

Do not substitute any of these components.

- TEVADAPTOR® Syringe Adaptor or OnGuard®2 CSTD Syringe Adaptor
- MEDALLION® COP or MEDALLION® Luer Lock syringe, 20 mL
- Ureteral Catheter with molded Luer lock port (5 Fr or 7 Fr)
- Uroject12 Syringe Lever
  Note: The Uroject12 Syringe Lever is a multi-use device and must be sterilized or disinfected before use. Please follow the sterilization or disinfection instructions detailed in the Uroject12 Syringe Lever Instructions for Use.
- An ice bath to chill the vial of JELMYTO prior to instillation.

TEVADAPTOR® or OnGuard®2 CSTD Syringe Adaptor

MEDALLION® COP or MEDALLION® Luer Lock syringe, 20 mL

Ureteral Catheter with molded Luer lock port

Uroject12 Syringe Lever

Ice Bath

Instillation Instructions

A. Measure the Kidney Volume
  The Instillation Volume will be equal to the patient's kidney volume. If the kidney volume is already known, proceed to Section B.
  If the kidney volume is NOT known, or needs to be reassessed, use the following steps:
  1. Perform a retrograde pyelogram using diluted contrast (50%) so that the entire renal pelvis and calyces are observed and contrast starts to flow below the ureteropelvic junction (UPJ).
  2. Record the volume of contrast injected at this point.
  3. Allow the contrast to drain from the kidney. This may take about five minutes.
    Note: Do not withdraw contrast back into the syringe.
  4. Repeat Steps 1 through 3 two more times, for a total of three measurements to improve accuracy.
  5. Average the three volume measurements and round to the nearest whole number. This is the patient's kidney volume.
B. Select the Instillation Volume
  Select the kidney volume OR 15 mL, whichever is lower, as the Instillation Volume.
  Note: Maximum Instillation Volume is 15 mL. Record this volume for future instillations.
C. Chill the JELMYTO
  1. Place the JELMYTO vial in the ice bath for at least 10 minutes, but no longer than one hour.
  2. After at least 10 minutes, advance the ureteral catheter over the guidewire towards the target anatomy in the pyelocalyceal system.

D. Prepare the Administration Syringe
  Once the vial is removed from the ice bath, you have 4 minutes to draw JELMYTO into the administration syringe before it solidifies.
  After 4 minutes, recap and place the components back in the ice bath for no more than 15 minutes to liquify the JELMYTO.
  1. Remove the JELMYTO vial from the ice bath and dry it off.
  2. Swirl the vial upright to ensure that JELMYTO is uniformly mixed.
  3. Connect the syringe adaptor to the 20 mL Luer Lock syringe. This will be the administration syringe.
  4. Slowly withdraw the calculated Instillation Volume of JELMYTO into the administration syringe.
  5. Press the "Clutch" button on the Uroject12 and pull the knob out.
  6. Insert the administration syringe into the Uroject12 Syringe Lever and rotate it clockwise until it locks in place.
  7. While pressing the "Clutch" button, advance the lever to just above the administration syringe's plunger.
    Immediately proceed with the instillation steps in Section E to avoid JELMYTO solidification.

E. Instill JELMYTO
  1. Remove the syringe adaptor from the administration syringe.
    Note: If JELMYTO gets on to the syringe tip or the catheter's Luer Lock port, wipe it off immediately with sterile gauze so it does not solidify and prevent a secure connection. (Refer to Frequently Asked Questions for further details.)
  2. Connect the administration syringe to the ureteral catheter's Luer Lock port, by rotating the syringe only.
  3. Using fluoroscopy, ensure the ureteral catheter is in the desired anatomical position.
  4. Gradually instill the JELMYTO into the patient by turning the knob at a rate of 1-2 seconds per stroke. The entire syringe must be emptied within one minute.
  5. Remove the ureteral catheter from the urinary tract.
  6. Remove the administration syringe from the Uroject12 by rotating the syringe barrel counter-clockwise.
  7. Discard the administration ancillaries according to your facility's disposal procedures.
  8. Send the Uroject12 to be reprocessed according to your facility's procedures and the Uroject12 Syringe Lever Instructions for Use.

Frequently Asked Questions:

How do I connect the syringe adaptor?
Screw the Luer Lock end of the syringe adaptor onto the syringe hub until it is finger tight.

How do I connect the syringe adaptor to the vial adaptor?
Place the syringe adaptor over the vial adaptor and align the tabs; then press down firmly. You will hear a snap which confirms successful attachment.

How do I disconnect the syringe adaptor from the vial adaptor?
Pinch the tabs on the syringe adaptor to separate it from the vial adaptor.

I am having a hard time working with reconstituted JELMYTO. It seems to be solidifying.
If you are having difficulty pushing or withdrawing JELMYTO, recap and place the components back into the ice bath until JELMYTO liquifies.

What should I do if there is JELMYTO spillage from the syringe tip?
You will need to clean JELMYTO off the syringe tip and the Luer Lock port of the catheter to ensure the two components can connect securely.

- To clean the syringe tip, fold a sterile gauze pad in half twice, and push it into the inside of the Luer Lock port to wipe any JELMYTO off the threads.
- To clean the Luer Lock port on the catheter, use a sterile gauze pad to wipe off any JELMYTO.

Verify that the connectors are clean to ensure a secure connection between the syringe and the catheter.

This "Instructions for Administration" has been approved by the U.S. Food and Drug Administration.

Distributed by:

UroGen Pharma, Inc.
Princeton, NJ 08540
www.JELMYTO.com

JELMYTO® and UroGen® are registered trademarks of UroGen Pharma, Ltd.
TEVADAPTOR® is a registered trademark of Simplivia Healthcare Ltd.
OnGuard® is a registered trademark of B. Braun Medical Inc.
MEDALLION® is a registered trademark of Merit Medical Systems, Inc.

Copyright© 2022 UroGen Pharma, Inc.
All rights reserved.

JEL-IFU-003

IFU-Phy-0006722/Ver. 5

PRINCIPAL DISPLAY PANEL - Kit Carton

NDC 72493-103-03

Jelmyto®
(mitomycin) for pyelocalyceal solution

Attention Pharmacist: Reconstitution
is required prior to dispensing.
See the Instructions for Pharmacy
before proceeding.

SINGLE-DOSE KIT

Warning: For Pyelocalyceal Use Only

Rx Only

Contents of Kit:

- 2 Vials of JELMYTO® (mitomycin) for pyelocalyceal solution, 40 mg per Vial
- 1 Vial Sterile Hydrogel, 20 mL per Vial
- 1 Admixture Label
- Full Prescribing Information
- Instructions for Pharmacy
- Instructions for Administration

Warning: Hazardous Drug

Store at 20°C to 25°C (68°F to 77°F); excursions permitted between 15°C and 30°C (59°F and 86°F).
Avoid excessive heat over 40°C (104°F). Protect from light.

Reconstituted JELMYTO should be instilled as soon as possible after reconstitution.
Store reconstituted JELMYTO at 20°C to 25°C (68°F to 77°F) for up to 96 hours (4 days).
Protect reconstituted JELMYTO from light.

When ready to instill, chill JELMYTO to -3°C to 5°C (27°F to 41°F) for at least 10 minutes,
but no longer than one hour, to revert it to a liquid form.

UroGen®
Pharma

PRINCIPAL DISPLAY PANEL - 40 mg Vial Label

NDC 72493-101-40

Single-Dose Vial
Sterile

Jelmyto®
(mitomycin) for pyelocalyceal solution
40 mg per Vial

See Instructions for Pharmacy for preparation instructions
Must be Reconstituted with Sterile Hydrogel Before Use
Warning: For Pyelocalyceal Use Only

Store at 20°C to 25°C (68°F to 77°F); excursions permitted
between 15°C and 30°C (59°F and 86°F). Avoid excessive heat
over 40°C (104°F). Protect from light.

Warning: Hazardous Drug

Rx Only

PRINCIPAL DISPLAY PANEL - 20 mL Vial Label

NDC 72493-102-20

Single-Dose Vial

Sterile Hydrogel

For use in preparation of JELMYTO™
(mitomycin) for pyelocalyceal solution

Not for Direct Administration

See Instructions for Pharmacy for
preparation instructions

Store at 20°C to 25°C (68°F to 77°F); excursions
permitted between 15°C and 30°C (59°F and 86°F).
Avoid excessive heat over 40°C (104°F).

Rx Only

20 mL per Vial